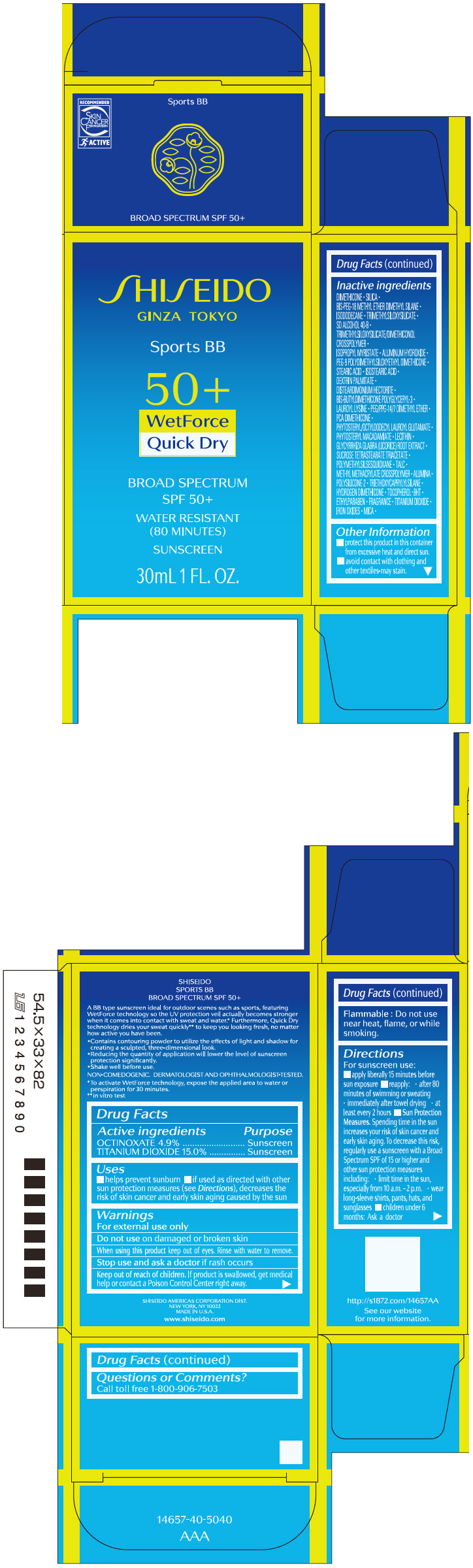 DRUG LABEL: SHISEIDO SPORTS BB DARK
NDC: 58411-536 | Form: EMULSION
Manufacturer: SHISEIDO AMERICAS CORPORATION
Category: otc | Type: HUMAN OTC DRUG LABEL
Date: 20260128

ACTIVE INGREDIENTS: OCTINOXATE 1.81545 g/30 mL; TITANIUM DIOXIDE 5.5575 g/30 mL
INACTIVE INGREDIENTS: DIMETHICONE; SILICON DIOXIDE; BIS-PEG-18 METHYL ETHER DIMETHYL SILANE; ISODODECANE; TRIMETHYLSILOXYSILICATE (M/Q 0.6-0.8); ALCOHOL; ISOPROPYL MYRISTATE; ALUMINUM HYDROXIDE; PEG-9 POLYDIMETHYLSILOXYETHYL DIMETHICONE; STEARIC ACID; ISOSTEARIC ACID; DEXTRIN PALMITATE (CORN; 20000 MW); DISTEARDIMONIUM HECTORITE; LAUROYL LYSINE; PEG/PPG-14/7 DIMETHYL ETHER; PHYTOSTERYL/OCTYLDODECYL LAUROYL GLUTAMATE; PHYTOSTERYL MACADAMIATE; GLYCYRRHIZA GLABRA; SUCROSE TETRASTEARATE TRIACETATE; POLYMETHYLSILSESQUIOXANE (4.5 MICRONS); TALC; METHYL METHACRYLATE/GLYCOL DIMETHACRYLATE CROSSPOLYMER; ALUMINUM OXIDE; TRIETHOXYCAPRYLYLSILANE; HYDROGEN DIMETHICONE (13 CST); .ALPHA.-TOCOPHEROL; BUTYLATED HYDROXYTOLUENE; ETHYLPARABEN; FERRIC OXIDE RED; FERRIC OXIDE YELLOW; FERROSOFERRIC OXIDE; MICA

SHISEIDO SPORTS BB DARK

Drug Facts

ACTIVE INGREDIENT

Active ingredients | Purpose
OCTINOXATE 4.9% | Sunscreen
TITANIUM DIOXIDE 15% | Sunscreen

Uses

- helps prevent sunburn
- if used as directed with other sun protection measures (see Directions), decreases the risk of skin cancer and early skin aging caused by the sun

Warnings

For external use only

Do not use on damaged or broken skin

WHEN USING

When using this productkeep out of eyes. Rinse with water to remove.

Stop use and ask a doctorif rash occurs.

Keep out of reach of children.If product is swallowed, get medical help or contact a Poison Control Center right away.

Flammable : Do not use near heat, flame, or while smoking.

Directions

- apply liberally 15 minutes before sun exposure
- reply
  - after 80 minutes after swimming and sweating
  - immediately after towel drying
  - at least every 2 hours
- Sun Protection Measures. Spending time in the sun increases your risk of skin cancer and early skin aging. To decrease this risk, regularly use a sunscreen with a Broad Spectrum SPF of 15 or higher and other un protection measures including:
  - limit time in the sun, especially from 10 a.m. – 2 p.m.
  - wear long-sleeve shirts, pants, hats, and sunglasses
  - children under 6 months: Ask a doctor

Inactive Ingredients

DIMETHICONE▪SILICA▪BIS-PEG-18 METHYL ETHER DIMETHYL SILANE▪ISODODECANE▪TRIMETHYLSILOXYSILICATE▪SD ALCOHOL 40-B▪TRIMETHYLSILOXYSILICATE/DIMETHICONOL CROSSPOLYMER▪ISOPROPYL MYRISTATE▪ALUMINUM HYDROXIDE▪PEG-9 POLYDIMETHYLSILOXYETHYL DIMETHICONE▪STEARIC ACID▪ISOSTEARIC ACID▪DEXTRIN PALMITATE▪DISTEARDIMONIUM HECTORITE▪BIS-BUTYLDIMETHICONE POLYGLYCERYL-3▪LAUROYL LYSINE▪PEG/PPG-14/7 DIMETHYL ETHER▪PCA DIMETHICONE▪PHYTOSTERYL/OCTYLDODECYL LAUROYL GLUTAMATE▪PHYTOSTERYL MACADAMIATE▪LECITHIN▪GLYCYRRHIZA GLABRA (LICORICE) ROOT EXTRACT▪SUCROSE TETRASTEARATE TRIACETATE▪POLYMETHYLSILSESQUIOXANE▪TALC▪METHYL METHACRYLATE CROSSPOLYMER▪ALUMINA▪POLYSILICONE-2▪TRIETHOXYCAPRYLYLSILANE▪HYDROGEN DIMETHICONE▪TOCOPHEROL▪BHT▪ETHYLPARABEN▪FRAGRANCE▪TITANIUM DIOXIDE▪IRON OXIDES▪MICA▪

Other information

- Protect this product in this container from excessive heat and direct sun.
- Avoid contact with clothing and other textiles
  - may stain.

Questions or comments?

Call toll free 1-800-906-7503

PRINCIPAL DISPLAY PANEL - 30 mL Bottle Carton

SHISEIDO
GINZA TOKYO

Sports BB

50+
WetForce
Quick Dry

BROAD SPECTRUM
SPF 50+

WATER RESISTANT
(80 MINUTES)

SUNSCREEN

30mL 1 FL. OZ.